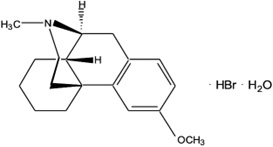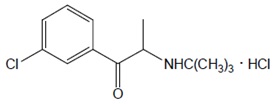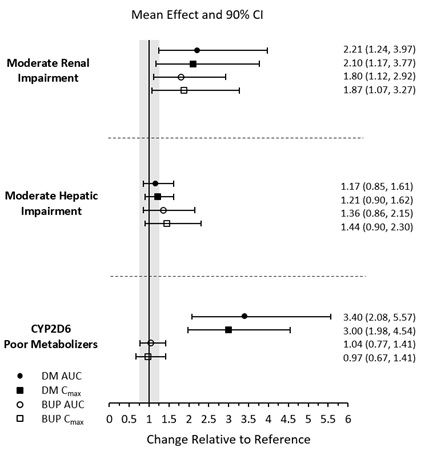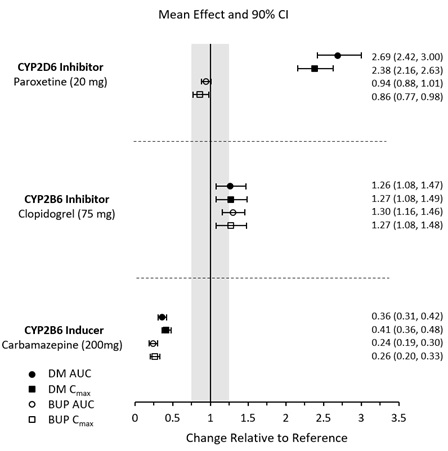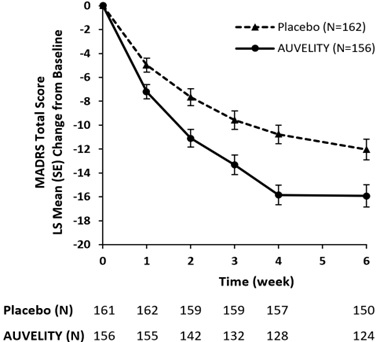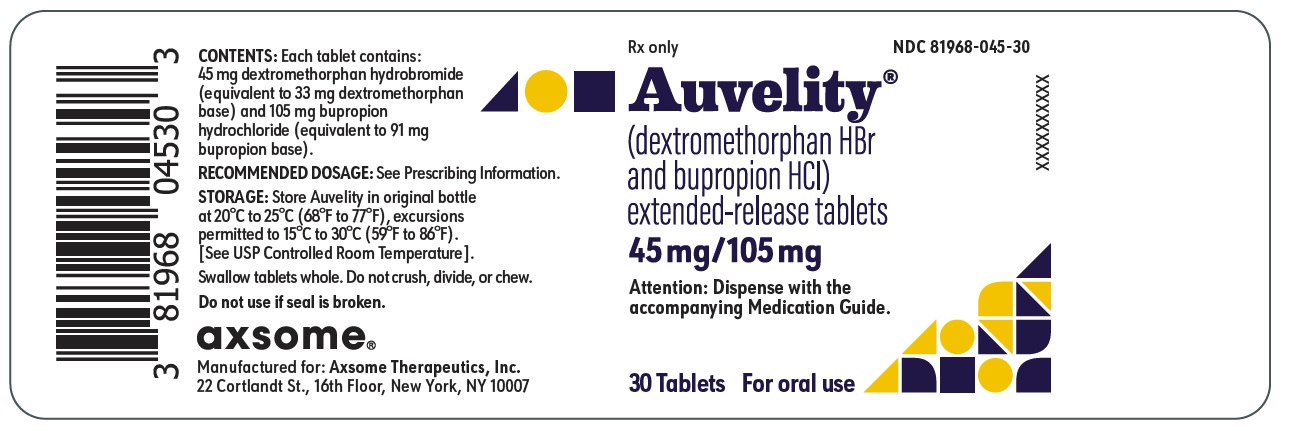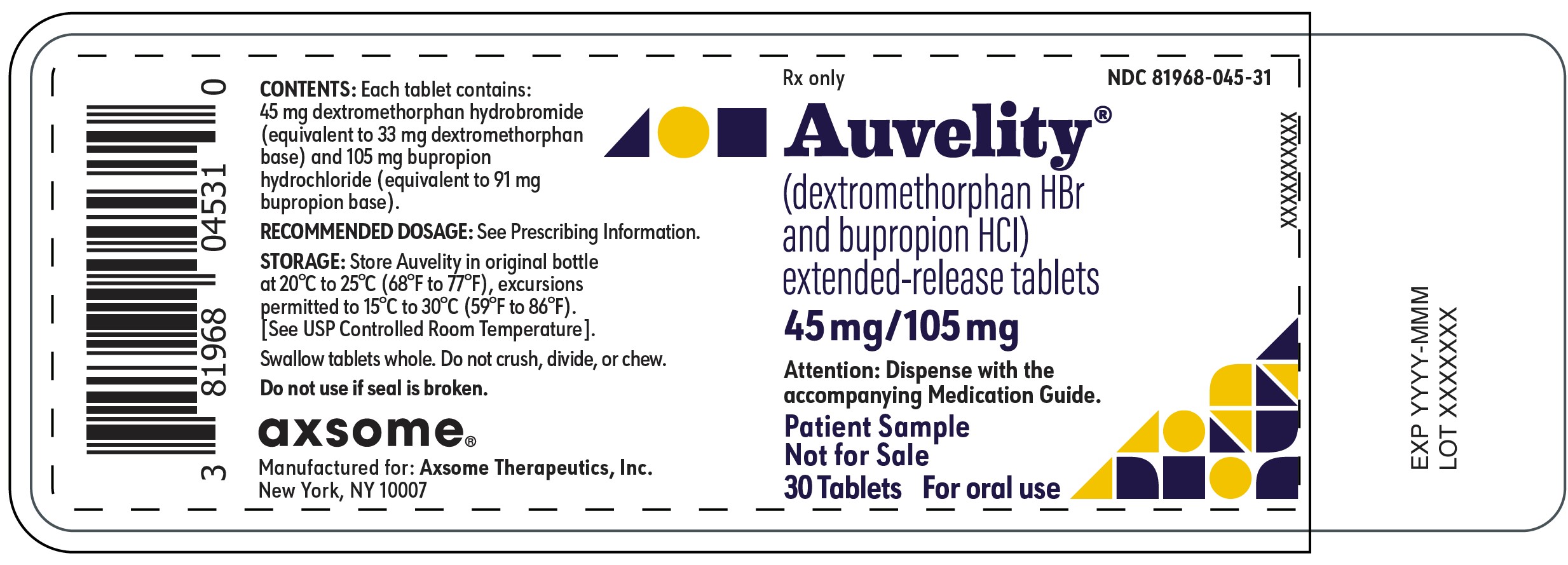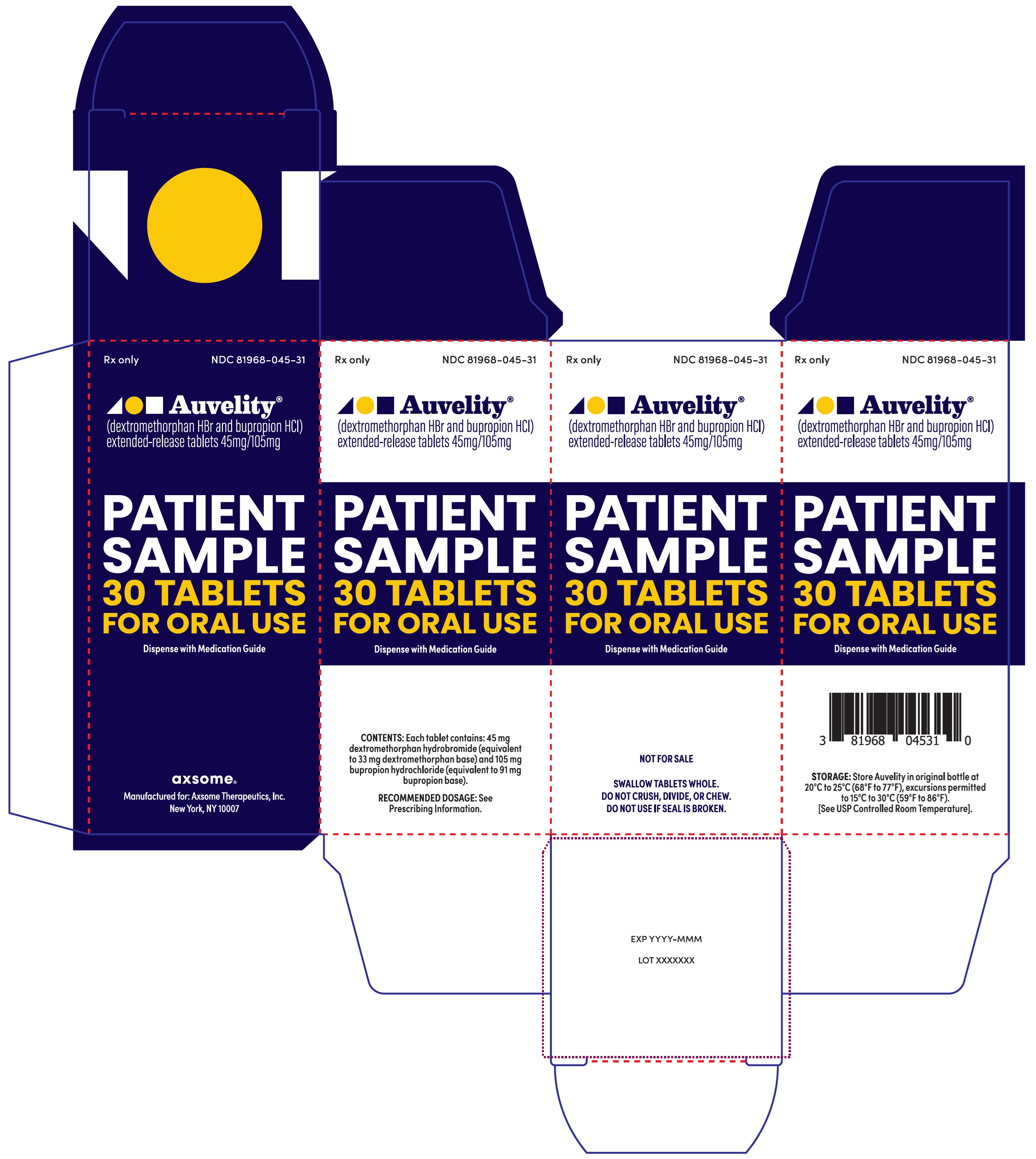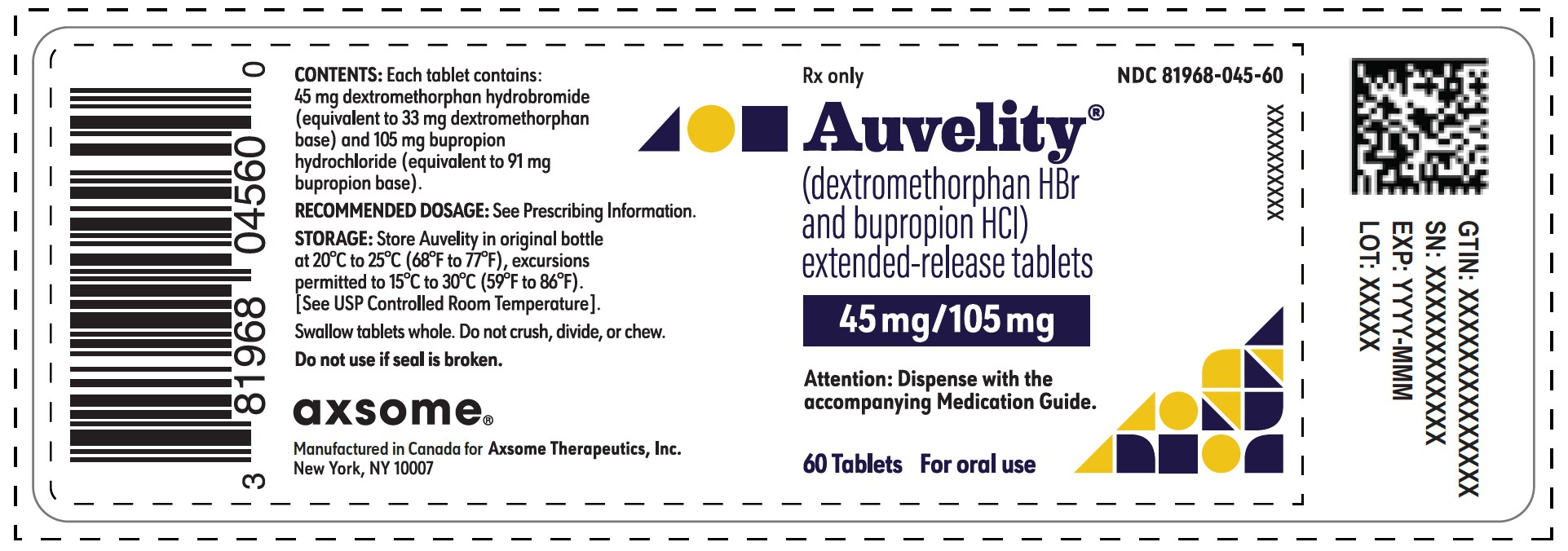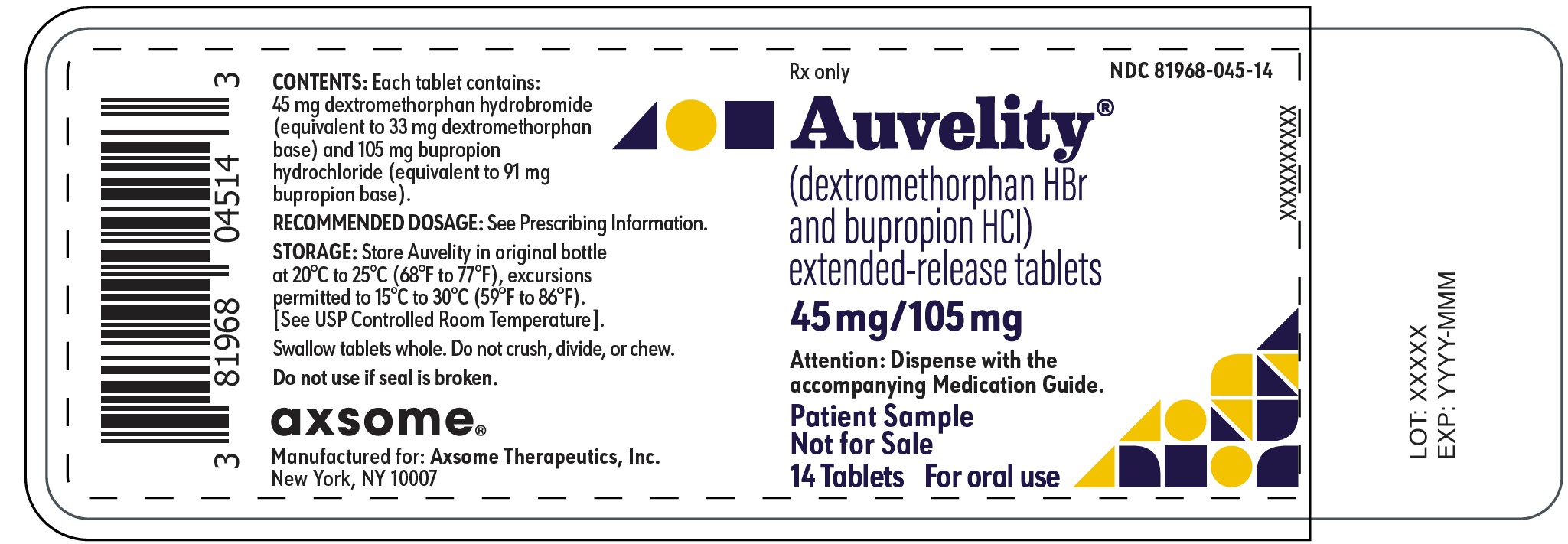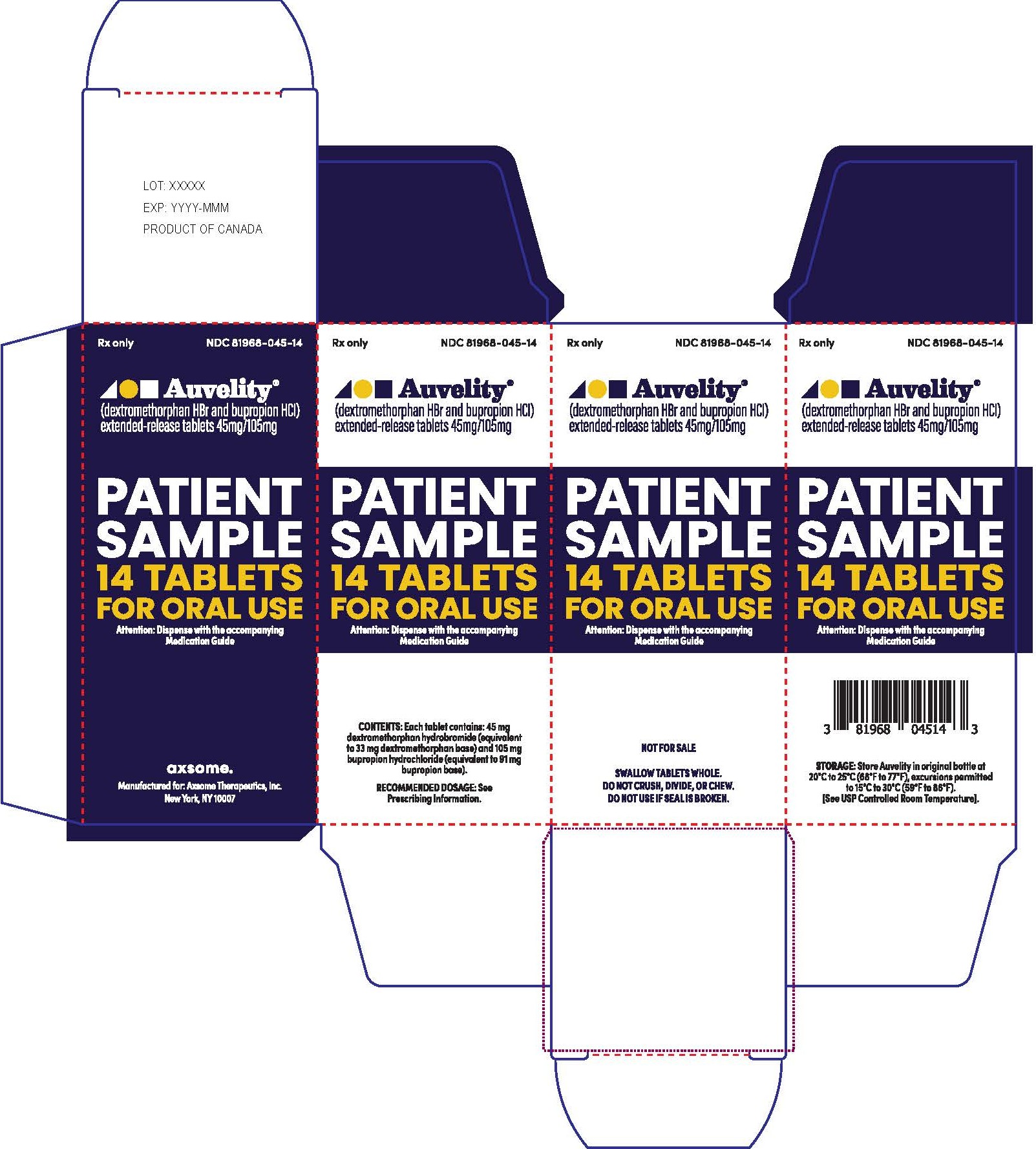 DRUG LABEL: AUVELITY
NDC: 81968-045 | Form: TABLET, MULTILAYER, EXTENDED RELEASE
Manufacturer: Axsome Therapeutics, Inc.
Category: prescription | Type: HUMAN PRESCRIPTION DRUG LABEL
Date: 20251231

ACTIVE INGREDIENTS: DEXTROMETHORPHAN HYDROBROMIDE 45 mg/1 1; BUPROPION HYDROCHLORIDE 105 mg/1 1
INACTIVE INGREDIENTS: CARBOMER HOMOPOLYMER, UNSPECIFIED TYPE; MICROCRYSTALLINE CELLULOSE; SILICON DIOXIDE; CROSPOVIDONE; GLYCERYL MONOCAPRYLATE; STEARIC ACID; MAGNESIUM STEARATE; CYSTEINE HYDROCHLORIDE; POLYVINYL ALCOHOL, UNSPECIFIED; FERRIC OXIDE RED; SODIUM LAURYL SULFATE; TITANIUM DIOXIDE; FERRIC OXIDE YELLOW; TALC

HIGHLIGHTS OF PRESCRIBING INFORMATION

These highlights do not include all the information needed to use AUVELITY safely and effectively. See full prescribing information for AUVELITY.
AUVELITY® (dextromethorphan hydrobromide and bupropion hydrochloride) extended-release tablets, for oral use
Initial U.S. Approval: 2022

WARNING: SUICIDAL THOUGHTS AND BEHAVIORS

See full prescribing information for complete boxed warning.

Increased risk of suicidal thoughts and behavior in pediatric and young adult patients taking antidepressants. Closely monitor all antidepressant-treated patients for clinical worsening and emergence of suicidal thoughts and behaviors. AUVELITY is not approved for use in pediatric patients. (5.1, 8.4)

1 INDICATIONS AND USAGE

AUVELITY is a combination of dextromethorphan, an uncompetitive N-methyl D-aspartate (NMDA) receptor antagonist and sigma-1 receptor agonist, and bupropion, an aminoketone and CYP450 2D6 inhibitor, indicated for the treatment of major depressive disorder (MDD) in adults. (1)

2 DOSAGE AND ADMINISTRATION

- Prior to initiating treatment with AUVELITY: assess blood pressure; screen patients for history of bipolar disorder, mania, or hypomania; and determine if patients are receiving any other medications that contain bupropion or dextromethorphan. (2.1)
- Starting dosage is one tablet once daily in the morning. After 3 days, increase to the maximum recommended dosage of one tablet twice daily, separated by at least 8 hours. Do not exceed two doses within the same day. (2.2)
- Swallow tablets whole, do not crush, divide, or chew. (2.2)
- Moderate renal impairment: One tablet by mouth once daily in the morning. (2.3, 8.6)
- CYP2D6 poor metabolizers: One tablet by mouth once daily in the morning. (2.5, 8.8, 12.3)

3 DOSAGE FORMS AND STRENGTHS

Extended-release tablets: 45 mg/105 mg dextromethorphan hydrobromide/ bupropion hydrochloride. (3)

4 CONTRAINDICATIONS

- Seizure disorder. (4)
- Current or prior diagnosis of bulimia or anorexia nervosa. (4)
- Abrupt discontinuation of alcohol, benzodiazepines, barbiturates, and antiepileptic drugs. (4)
- Use with an MAOI or within 14 days of stopping treatment with AUVELITY. Do not use AUVELITY within 14 days of discontinuing an MAOI. (4)
- Known hypersensitivity to bupropion, dextromethorphan, or other components of AUVELITY. (4)

5 WARNINGS AND PRECAUTIONS

- Seizure: Risk is dose-related. Discontinue if seizure occurs. (4, 5.2)
- Increased Blood Pressure and Hypertension: AUVELITY can increase blood pressure and cause hypertension. Assess blood pressure before initiating treatment and monitor periodically during treatment. (5.3)
- Activation of Mania or Hypomania: Screen patients for bipolar disorder. (5.4)
- Psychosis and Other Neuropsychiatric Reactions: Instruct patients to contact a healthcare provider if such reactions occur. (5.5)
- Angle-Closure Glaucoma: Angle-closure glaucoma has occurred in patients with untreated anatomically narrow angles treated with antidepressants. (5.6)
- Dizziness: AUVELITY may cause dizziness. Take precautions to reduce falls and use caution when operating machinery. (5.7)
- Serotonin Syndrome: Use of AUVELITY with selective serotonin reuptake inhibitors (SSRIs) or tricyclic antidepressants increases the risk. Discontinue if occurs. (5.8, 7.1)
- Embryo-fetal Toxicity: May cause fetal harm. Advise pregnant females of the potential risk to a fetus. Discontinue treatment in pregnant females and use alternative treatment for females who are planning to become pregnant. (5.9, 8.1, 8.3)

6 ADVERSE REACTIONS

Most common adverse reactions (≥5% and more than twice as frequently as placebo): dizziness, headache, diarrhea, somnolence, dry mouth, sexual dysfunction, and hyperhidrosis. (6.1)

To report SUSPECTED ADVERSE REACTIONS, contact Axsome Therapeutics at 1-800-484-1672 or FDA at 1-800-FDA-1088 or www.fda.gov/medwatch.

7 DRUG INTERACTIONS

- Strong CYP2D6 inhibitors: Recommended dosage is one tablet by mouth once daily in the morning. (2.4, 7.1)
- Strong CYP2B6 inducers: Avoid use. (7.1)
- CYP2D6 Substrates: Increases the exposures of drugs that are substrates of CYP2D6. (7.1)
- Digoxin: May decrease plasma digoxin levels. Monitor digoxin levels. (7.1)
- Drugs that lower seizure threshold: Coadministration may increase risk of seizure. (7.1)
- Dopaminergic drugs: Central Nervous System (CNS) toxicity can occur with concomitant use. (7.1)
- Drug-laboratory test interactions: AUVELITY can cause false-positive urine test results for amphetamines. (7.2)

8 USE IN SPECIFIC POPULATIONS

- Lactation: Breastfeeding not recommended. (8.2)
- Severe Renal Impairment: Avoid use. (8.6)
- Severe Hepatic Impairment: Avoid use. (8.7)

FULL PRESCRIBING INFORMATION

WARNING: SUICIDAL THOUGHTS AND BEHAVIORS

Antidepressants increased the risk of suicidal thoughts and behaviors in pediatric and young adult patients in short-term studies. Closely monitor all antidepressant-treated patients for clinical worsening, and emergence of suicidal thoughts and behaviors [see Warnings and Precautions (5.1)]. AUVELITY is not approved for use in pediatric patients [see Use in Specific Populations (8.4)].

1 INDICATIONS AND USAGE

AUVELITY is indicated for the treatment of major depressive disorder (MDD) in adults.

2 DOSAGE AND ADMINISTRATION

2.1 Important Recommendations Prior to Initiating and During Treatment with AUVELITY

Prior to initiating and during treatment with AUVELITY:

- assess blood pressure and monitor periodically during treatment [see Warnings and Precautions (5.3)].
- screen patients for a personal or family history of bipolar disorder, mania, or hypomania [see Warnings and Precautions (5.4)].
- screen patients to determine if they are receiving any other medications that contain bupropion or dextromethorphan [see Warnings and Precautions (5.2, 5.5, 5.8)].

2.2 Recommended Dosage for the Treatment of Major Depressive Disorder

The recommended starting dosage of AUVELITY (45 mg of dextromethorphan hydrobromide and 105 mg of bupropion hydrochloride) is one tablet once daily in the morning. After 3 days, increase to the maximum recommended dosage of one tablet twice daily, given at least 8 hours apart. Do not exceed two doses within the same day.

Administer AUVELITY orally with or without food [see Clinical Pharmacology (12.3)]. Swallow tablets whole, do not crush, divide, or chew.

2.3 Dosage Recommendations in Patients with Renal Impairment

The recommended dosage of AUVELITY for patients with moderate renal impairment (eGFR 30 to 59 mL/minute/1.73 m^2) is one tablet once daily in the morning [see Use in Specific Populations (8.6), Clinical Pharmacology (12.3)].

2.4 Dosage Recommendations for Concomitant Use with Strong CYP2D6 Inhibitors

The recommended dosage of AUVELITY when co-administered with strong CYP2D6 inhibitors is one tablet once daily in the morning [see Drug Interactions (7.1), Clinical Pharmacology (12.3)].

2.5 Dosage Recommendations for Known CYP2D6 Poor Metabolizers (PMs)

The recommended dosage for patients known to be poor CYP2D6 metabolizers is one tablet once daily in the morning [see Use in Specific Populations (8.8), Clinical Pharmacology (12.3)].

2.6 Switching a Patient to or from a Monoamine Oxidase Inhibitor (MAOI) Antidepressant

At least 14 days must elapse between discontinuation of an MAOI intended to treat depression and initiation of therapy with AUVELITY. Conversely, at least 14 days must be allowed after stopping AUVELITY before starting an MAOI antidepressant [see Contraindications (4), Drug Interactions (7.1)].

3 DOSAGE FORMS AND STRENGTHS

AUVELITY extended-release tablets contain 45 mg dextromethorphan hydrobromide and 105 mg bupropion hydrochloride. The tablets are beige and round with “45/105” debossed on one side.

4 CONTRAINDICATIONS

AUVELITY is contraindicated in patients:

- with a seizure disorder [see Warnings and Precautions (5.2)].
- with a current or prior diagnosis of bulimia or anorexia nervosa as a higher incidence of seizures was observed in such patients treated with the immediate-release formulation of bupropion [see Warnings and Precautions (5.2)].
- undergoing abrupt discontinuation of alcohol, benzodiazepines, barbiturates, and antiepileptic drugs [see Warnings and Precautions (5.2), Drug Interactions (7.1)].
- taking, or within 14 days of stopping, MAOIs due to the risk of serious and possibly fatal drug interactions, including hypertensive crisis and serotonin syndrome [see Dosage and Administration (2.6), Warnings and Precautions (5.8), Drug Interactions (7.1)]. Starting AUVELITY in a patient treated with reversible MAOIs such as linezolid or intravenous methylene blue is contraindicated.
- with known hypersensitivity to bupropion, dextromethorphan, or other components of AUVELITY. Anaphylactoid/anaphylactic reactions and Stevens-Johnson syndrome have been reported with bupropion. Arthralgia, myalgia, fever with rash, and other serum sickness-like symptoms suggestive of delayed hypersensitivity have also been reported with bupropion [see Adverse Reactions (6.2)].

5 WARNINGS AND PRECAUTIONS

5.1 Suicidal Thoughts and Behaviors in Adolescents and Young Adults

In pooled analyses of placebo-controlled trials of antidepressant drugs (SSRIs and other antidepressant classes) that included approximately 77,000 adult patients and 4,500 pediatric patients, the incidence of suicidal thoughts and behaviors in antidepressant-treated patients age 24 years and younger was greater than in placebo-treated patients. There was considerable variation in risk of suicidal thoughts and behaviors among drugs, but there was an increased risk identified in young patients for most drugs studied. There were differences in absolute risk of suicidal thoughts and behaviors across the different indications, with the highest incidence in patients with MDD. The drug-placebo differences in the number of cases of suicidal thoughts and behaviors per 1000 patients treated are provided in Table 1.

Table 1: Risk Differences of the Number of Patients of Suicidal Thoughts and Behavior in the Pooled Placebo-Controlled Trials of Antidepressants in Pediatric* and Adult Patients
Age Range | Drug-Placebo Difference in Number of Patients of Suicidal Thoughts or Behaviors per 1000 Patients Treated
 | Increases Compared to Placebo
<18 years old | 14 additional patients
18-24 years old | 5 additional patients
 | Decreases Compared to Placebo
25-64 years old | 1 fewer patient
≥65 years old | 6 fewer patients
*AUVELITY is not approved for use in pediatric patients.

It is unknown whether the risk of suicidal thoughts and behaviors in children, adolescents, and young adults extends to longer-term use, i.e., beyond four months. However, there is substantial evidence from placebo-controlled maintenance studies in adults with MDD that antidepressants delay the recurrence of depression and that depression itself is a risk factor for suicidal thoughts and behaviors.

Monitor all antidepressant-treated patients for any indication for clinical worsening and emergence of suicidal thoughts and behaviors, especially during the initial few months of drug therapy, and at times of dosage changes. Counsel family members or caregivers of patients to monitor for changes in behavior and to alert the healthcare provider. Consider changing the therapeutic regimen, including possibly discontinuing AUVELITY, in patients whose depression is persistently worse, or who are experiencing emergent suicidal thoughts or behaviors.

5.2 Seizure

Bupropion, a component of AUVELITY, can cause seizure. The risk of seizure with bupropion is dose-related.

When a bupropion hydrochloride (HCl) sustained-release tablet was dosed up to 300 mg per day (approximately 1.5 times the maximum recommended daily dosage of AUVELITY), the incidence of seizure was approximately 0.1% (1/1,000) and increased to approximately 0.4% (4/1,000) at the maximum recommended dosage for the sustained-release tablet of 400 mg per day (approximately 2 times the maximum recommended daily dosage of AUVELITY).

The risk of seizures is also related to patient factors, clinical situations, and concomitant medications that lower the seizure threshold. Consider these risks before initiating treatment with AUVELITY. AUVELITY is contraindicated in patients with a seizure disorder, current or prior diagnosis of anorexia nervosa or bulimia, or undergoing abrupt discontinuation of alcohol, benzodiazepines, barbiturates, and antiepileptic drugs [see Contraindications (4), Drug Interactions (7.1)]. The following conditions can also increase the risk of seizure: severe head injury; arteriovenous malformation; CNS tumor or CNS infection; severe stroke; concomitant use of other medications that lower the seizure threshold (e.g., other bupropion products, antipsychotics, tricyclic antidepressants, theophylline, and systemic corticosteroids); metabolic disorders (e.g., hypoglycemia, hyponatremia, severe hepatic impairment, and hypoxia); use of illicit drugs (e.g., cocaine); or abuse or misuse of prescription drugs such as CNS stimulants. Additional predisposing conditions include diabetes mellitus treated with oral hypoglycemic drugs or insulin; use of anorectic drugs; and excessive use of alcohol, benzodiazepines, sedative/hypnotics, or opiates.

Because the risk of seizure with bupropion is dose-related, screen patients for use of other bupropion-containing products prior to initiating AUVELITY [see Dosage and Administration (2.1)]. If concomitant use of AUVELITY with other bupropion-containing products is clinically warranted, inform patients of the risk. Discontinue AUVELITY and do not restart treatment if the patient experiences a seizure.

5.3 Increased Blood Pressure and Hypertension

AUVELITY contains bupropion, which can cause elevated blood pressure and hypertension. The risk of hypertension is increased if AUVELITY is used concomitantly with MAOIs or other drugs that increase dopaminergic or noradrenergic activity [see Contraindications (4), Drug Interactions (7.1)].

Data from a comparative trial of a sustained-release tablet formulation of bupropion HCl, nicotine transdermal system (NTS), the combination of sustained-release bupropion plus NTS, and placebo as an aid to smoking cessation suggest a higher incidence of hypertension in patients treated with the combination of sustained-release bupropion and NTS. In this trial, 6.1% of subjects treated with the combination of sustained-release bupropion and NTS had hypertension compared with 2.5%, 1.6%, and 3.1% of subjects treated with sustained-release bupropion, NTS, and placebo, respectively. The majority of these subjects had evidence of pre-existing hypertension. Three subjects (1.2%) treated with the combination of sustained-release bupropion and NTS and 1 subject (0.4%) treated with NTS had study medication discontinued due to hypertension compared with none of the subjects treated with sustained-release bupropion or placebo. Monitor blood pressure in patients who receive the combination of bupropion and nicotine replacement.

In a clinical trial of an immediate-release bupropion tablet formulation in MDD subjects with stable congestive heart failure (N=36), bupropion was associated with an exacerbation of pre-existing hypertension in 2 subjects, leading to discontinuation of bupropion treatment. There are no controlled trials assessing the safety of bupropion in patients with a recent history of myocardial infarction or unstable cardiac disease.

Assess blood pressure prior to initiating treatment, and periodically monitor blood pressure during treatment with AUVELITY [see Dosage and Administration (2.1)].

5.4 Activation of Mania or Hypomania

Antidepressant treatment can precipitate a manic, mixed, or hypomanic manic episode. The risk appears to be increased in patients with bipolar disorder or who have risk factors for bipolar disorder. Prior to initiating AUVELITY, screen patients for a history of bipolar disorder and the presence of risk factors for bipolar disorder (e.g., family history of bipolar disorder, suicide, or depression) [see Dosage and Administration (2.1)]. AUVELITY is not approved for use in treating bipolar depression.

5.5 Psychosis and Other Neuropsychiatric Reactions

AUVELITY contains bupropion. Depressed patients treated with bupropion have had a variety of neuropsychiatric signs and symptoms, including delusions, hallucinations, psychosis, concentration disturbance, paranoia, and confusion. Some of these patients had a diagnosis of bipolar disorder. In some cases, these symptoms abated upon dose reduction and/or withdrawal of treatment.

AUVELITY contains dextromethorphan. Dextromethorphan overdose can cause toxic psychosis, stupor, coma, and hyperexcitability [see Overdosage (10)].

Because the risks of neuropsychiatric reactions are dose-related, screen patients for use of other bupropion- or dextromethorphan-containing products prior to initiating AUVELITY. If concomitant use of AUVELITY with other bupropion- or dextromethorphan-containing products is clinically warranted, monitor patients for neuropsychiatric reactions [see Dosage and Administration (2.1)] and instruct patients to contact a healthcare provider if such reactions occur.

5.6 Angle-Closure Glaucoma

The pupillary dilation that occurs following use of many antidepressant drugs including bupropion, a component of AUVELITY, may trigger an angle closure attack in a patient with anatomically narrow angles who does not have a patent iridectomy. Avoid use of antidepressants, including AUVELITY, in patients with untreated anatomically narrow angles.

5.7 Dizziness

AUVELITY may cause dizziness [see Adverse Reactions (6.1)]. In controlled studies of AUVELITY, 14% of patients receiving AUVELITY and 6% of patients on placebo experienced dizziness. Take precautions to reduce the risk of falls, particularly for patients with motor impairment affecting gait or those with a history of falls. Caution patients about operating hazardous machinery, including motor vehicles, until they are reasonably certain that AUVELITY therapy does not affect them adversely.

5.8 Serotonin Syndrome

AUVELITY contains dextromethorphan. Concomitant use of AUVELITY with SSRIs or tricyclic antidepressants may cause serotonin syndrome, a potentially life-threatening condition with changes including altered mental status, hypertension, restlessness, myoclonus, hyperthermia, hyperreflexia, diaphoresis, shivering, and tremor [see Drug Interactions (7.1), Overdosage (10)].

The concomitant use of AUVELITY with MAOIs is contraindicated. In addition, do not initiate AUVELITY in a patient being treated with MAOIs such as linezolid or intravenous methylene blue. If it is necessary to initiate treatment with an MAOI such as linezolid or intravenous methylene blue in a patient taking AUVELITY discontinue AUVELITY before initiating treatment with the MAOI [see Contraindications (4), Drug Interactions (7)].

Prior to initiating AUVELITY, screen patients for use of other dextromethorphan-containing products [see Dosage and Administration (2.1)]. If concomitant use of AUVELITY with other serotonergic drugs is clinically warranted, inform patients of the increased risk for serotonin syndrome and monitor for symptoms. Discontinue AUVELITY and/or concomitant serotonergic drug immediately if the above symptoms occur, and initiate supportive symptomatic treatment.

5.9 Embryo-fetal Toxicity

Based on animal studies, AUVELITY may cause fetal harm when administered during pregnancy. In developmental toxicity studies in rats and rabbits, when a combination of dextromethorphan/quinidine was given to pregnant animals, fetal malformations (rabbits) and embryolethality were demonstrated in offspring. Neurotoxicity findings were observed in juvenile rats treated with a combination of dextromethorphan/quinidine on postnatal day (PND) 7, which corresponds to the third trimester of gestation through the first few months of life and may extend through the first three years of life in humans. The separate effect of dextromethorphan on developmental toxicity at the recommended clinical dose is unclear. Discontinue treatment in pregnant females and advise the patient about the potential risk to a fetus. Use alternative treatment for females who are planning to become pregnant [see Use in Specific Populations (8.1, 8.3)].

6 ADVERSE REACTIONS

The following adverse reactions are discussed in more detail in other sections of the labeling:

- Suicidal Thoughts and Behaviors in Adolescents and Young Adults [see Warnings and Precautions (5.1)]
- Seizure [see Warnings and Precautions (5.2)]
- Increased Blood Pressure and Hypertension [see Warnings and Precautions (5.3)]
- Activation of Mania or Hypomania [see Warnings and Precautions (5.4)]
- Psychosis and Other Neuropsychiatric Reactions [see Warnings and Precautions (5.5)]
- Angle-closure Glaucoma [see Warnings and Precautions (5.6)]
- Dizziness [see Warnings and Precautions (5.7)]
- Serotonin Syndrome [see Warnings and Precautions (5.8)]
- Embryo-fetal Toxicity [see Warnings and Precautions (5.9)]

6.1 Clinical Trials Experience

Because clinical trials are conducted under widely varying conditions, adverse reaction rates observed in the clinical trials of a drug cannot be directly compared to rates in the clinical trials of another drug and may not reflect the rates observed in clinical practice.

AUVELITY was evaluated for safety in a total of 1114 patients with MDD or another indication from four studies (two 6-week studies in MDD, one 6-week study in another indication, and one long-term study in MDD and another indication). One 6-week study in MDD employed placebo as a control arm. Two 6-week studies, one in MDD and one in another indication, employed bupropion as a control arm. In the patients treated with AUVELITY in the long-term study (n=876), 597 received at least 6 months of treatment, and 110 received at least 12 months of treatment.

The data below are based on the 6-week, placebo-controlled study in which either AUVELITY (n=162) or placebo (n=164) was administered twice daily to patients with MDD (Study 1). Demographics of the patients who participated in this study are summarized in Clinical Studies [see Clinical Studies (14)].

Adverse Reactions Leading to Discontinuation

In the 6-week placebo-controlled study, 4% of patients treated with AUVELITY and 0% of placebo-treated patients discontinued participation due to adverse reactions. The adverse reaction that led to study discontinuation in ≥1% of patients treated with AUVELITY was anxiety (2%).

Most Common Adverse Reactions

In the 6-week placebo-controlled clinical study, the most common (incidence ≥5% for AUVELITY and more than twice as frequently as placebo) adverse reactions were dizziness (16%), headache (8%), diarrhea (7%), somnolence (7%), dry mouth (6%), sexual dysfunction (6%), and hyperhidrosis (5%).

Table 2 shows the incidence of adverse reactions that occurred in ≥2% of patients treated with AUVELITY and more frequently than in patients treated with placebo in Study 1.

Table 2: Adverse Reactions Occurring in ≥ 2% of Adult Patients with MDD Treated with AUVELITY and More Frequently than in Patients Treated with Placebo in a 6-Week Placebo-Controlled Study (Study 1)
Adverse Reaction | AUVELITY (N=162); % | Placebo (N=164); %
Dizziness | 16 | 6
Nausea | 13 | 9
Headache | 8 | 4
Diarrhea | 7 | 3
Somnolence | 7 | 3
Dry mouth | 6 | 2
Sexual dysfunctiona | 6 | 0
Hyperhidrosis | 5 | 0
Anxiety | 4 | 1
Constipation | 4 | 2
Decreased appetite | 4 | 1
Insomnia | 4 | 2
Arthralgia | 3 | 0
Fatigueb | 3 | 2
Paraesthesiac | 3 | 0
Vision blurred | 3 | 0
aSexual dysfunction includes orgasm abnormal, erectile dysfunction, libido decreased, anorgasmia
bFatigue includes fatigue, lethargy
cParaesthesia includes paraesthesia, hypoaesthesia

6.2 Postmarketing Experience

The following adverse reactions have been identified with the use of the individual components of AUVELITY, dextromethorphan and bupropion, during postmarketing use. Because these reactions are reported voluntarily from a population of uncertain size, it is not always possible to reliably estimate their frequency or establish a causal relationship to drug exposure.

Dextromethorphan

Drowsiness, dizziness, nervousness or restlessness, nausea, vomiting, and stomach pain.

Bupropion

Body (General): Arthralgia, myalgia, and fever with rash and other symptoms suggestive of delayed hypersensitivity. These symptoms may resemble serum sickness.

Cardiovascular: Complete atrioventricular block, extrasystoles, hypotension, hypertension (in some cases severe), phlebitis, pulmonary embolism, and Brugada pattern/syndrome.

Digestive: Colitis, esophagitis, gastrointestinal hemorrhage, gum hemorrhage, hepatitis, intestinal perforation, pancreatitis, and stomach ulcer.

Endocrine: Hyperglycemia, hypoglycemia, hyponatremia, and syndrome of inappropriate antidiuretic hormone secretion.

Hemic and Lymphatic: Anemia, leukocytosis, leukopenia, lymphadenopathy, pancytopenia, and thrombocytopenia. Altered PT and/or INR, infrequently associated with hemorrhagic or thrombotic complications, were observed when bupropion was coadministered with warfarin.

Metabolic and Nutritional: Glycosuria.

Musculoskeletal: Muscle rigidity/fever/rhabdomyolysis and muscle weakness.

Nervous System: Abnormal electroencephalogram (EEG), aggression, agitation, akinesia, aphasia, coma, completed suicide, delirium, delusions, depression, dysarthria, euphoria, extrapyramidal syndrome (dyskinesia, dystonia, hypokinesia, parkinsonism), hallucinations, homicidal ideation, hostility, increased libido, manic reaction, neuralgia, neuropathy, panic, paranoid ideation, psychosis, restlessness, suicide ideation, suicide attempt, unmasking tardive dyskinesia, and aseptic meningitis.

Respiratory: Pneumonia.

Skin and subcutaneous tissue disorders: Alopecia, angioedema, exfoliative dermatitis, hirsutism, Stevens-Johnson syndrome, acute generalized exanthematous pustulosis, and drug reaction with eosinophilia and systemic symptoms (DRESS).

Special Senses: Deafness, increased intraocular pressure, and mydriasis.

Urogenital: Abnormal ejaculation, cystitis, dyspareunia, dysuria, gynecomastia, menopause, painful erection, salpingitis, urinary incontinence, urinary retention, and vaginitis.

7 DRUG INTERACTIONS

7.1 Drugs Having Clinically Important Interactions with AUVELITY

Table 3: Clinically Important Drug Interactions with AUVELITY
Monoamine Oxidase Inhibitors (MAOIs)
Clinical Impact | Concomitant use of AUVELITY with MAOIs increases the risk of hypertensive crisis and serotonin syndrome.
Intervention | AUVELITY is contraindicated in patients taking MAOIs (including MAOIs such as linezolid or intravenous methylene blue) or in patients who have taken MAOIs within the preceding 14 days. Allow at least 14 days after stopping AUVELITY before starting an MAOI [see Dosage and Administration (2.6), Contraindications (4), Warnings and Precautions (5.3, 5.8)]
Serotonergic Drugs
Clinical Impact | Concomitant use of AUVELITY with other serotonergic drugs increases the risk of serotonin syndrome.
Intervention | Monitor for symptoms of serotonin syndrome when AUVELITY is used concomitantly with other drugs that may affect the serotonergic neurotransmitter systems. If serotonin syndrome occurs, consider discontinuation of AUVELITY and/or concomitant serotonergic drug [see Dosage and Administration (2.1), Warnings and Precautions (5.8)].
Drugs that Lower Seizure Threshold
Clinical Impact | AUVELITY contains bupropion which can cause seizure. Co-administration with other drugs that lower seizure threshold may increase risk of seizure.
Intervention | Use caution when administering AUVELITY concomitantly with drugs that lower the seizure threshold [see Warnings and Precautions (5.2)]. Discontinue AUVELITY and do not restart treatment if the patient experiences a seizure.
Strong Inhibitors of CYP2D6
Clinical Impact | Concomitant use of AUVELITY with strong CYP2D6 inhibitors increases plasma concentrations of dextromethorphan.
Intervention | Dosage adjustment is necessary when AUVELITY is co-administered with strong inhibitors of CYP2D6 [see Dosage and Administration (2.4)]. Monitor patients for adverse reactions potentially attributable to dextromethorphan, such as somnolence and dizziness.
Strong Inducers of CYP2B6
Clinical Impact | Concomitant use of AUVELITY with strong CYP2B6 inducers decreases plasma concentrations of dextromethorphan and bupropion and may decrease efficacy of AUVELITY [see Clinical Pharmacology (12.3)].
Intervention | Avoid co-administration of AUVELITY with strong inducers of CYP2B6. Consider alternatives to strong CYP2B6 inducers if needed.
Drugs Metabolized by CYP2D6
Clinical Impact | CYP2D6 Substrates Coadministration of AUVELITY with drugs that are metabolized by CYP2D6 can increase the exposures of drugs that are substrates of CYP2D6.; Drugs that Require Metabolic Activation by CYP2D6 Drugs that require metabolic activation by CYP2D6 to be effective could have reduced efficacy when administered concomitantly with AUVELITY.
Intervention | CYP2D6 Substrates When used concomitantly with AUVELITY, it may be necessary to decrease the dose of CYP2D6 substrates, particularly for drugs with a narrow therapeutic index.; Drugs that Require Metabolic Activation by CYP2D6 Patients treated concomitantly with AUVELITY may require increased doses of drugs that require activation by CYP2D6 to be effective.
Digoxin
Clinical Impact | Coadministration of AUVELITY with digoxin may decrease plasma digoxin levels.
Intervention | Monitor plasma digoxin levels in patients treated concomitantly with AUVELITY and digoxin [see Clinical Pharmacology (12.3)].
Dopaminergic Drugs
Clinical Impact | CNS toxicity was reported when bupropion was co-administered with levodopa or amantadine. Adverse reactions include restlessness, agitation, tremor, ataxia, gait disturbance, vertigo, and dizziness.
Intervention | Use caution when administering AUVELITY concomitantly with dopaminergic drugs.
Alcohol
Clinical Impact | AUVELITY contains bupropion which can increase adverse neuropsychiatric events or reduce alcohol tolerance.
Intervention | Consumption of alcohol should be minimized or avoided during treatment with AUVELITY.

7.2 Drug-Laboratory Test Interactions

False-positive urine immunoassay screening tests for amphetamines have been reported in patients taking bupropion. This is due to lack of specificity of some screening tests. False positive test results may result even following discontinuation of bupropion therapy. Confirmatory tests, such as gas chromatography/mass spectrometry, will distinguish bupropion from amphetamines.

8 USE IN SPECIFIC POPULATIONS

8.1 Pregnancy

Pregnancy Exposure Registry

There is a pregnancy exposure registry that monitors pregnancy outcomes in women exposed to antidepressants, including AUVELITY, during pregnancy. Healthcare providers are encouraged to register patients by contacting the National Pregnancy Registry for Antidepressants at 1-866-961-2388 or online at: https://womensmentalhealth.org/research/pregnancyregistry/antidepressants/.

Risk Summary

Based on animal studies, AUVELITY may cause fetal harm when administered during pregnancy. AUVELITY is not recommended during pregnancy. If a female becomes pregnant while being treated with AUVELITY, discontinue treatment and counsel the patient about the potential risk to a fetus [see Warnings and Precautions (5.9)].

In oral studies conducted in rats and rabbits, a combination of dextromethorphan/quinidine demonstrated developmental toxicity, including fetal malformations (rabbits) and embryolethality, when given to pregnant animals. When bupropion alone was administered to pregnant rats during organogenesis, there was no evidence of fetal malformations at doses up to approximately 21 times the maximum recommended human dose (MRHD) of 210 mg/day. When bupropion alone was given to pregnant rabbits during organogenesis, non-dose–related increases in incidence of fetal malformations, and skeletal variations were observed at doses approximately 2 to 5 times the MRHD and greater. Decreased fetal weights were seen at bupropion doses approximately 5 times the MRHD and greater. Neurotoxicity findings were observed in juvenile rats treated with a combination of dextromethorphan/quinidine on postnatal day (PND) 7, which corresponds to the third trimester of gestation through the first few months of life and may extend through the first three years of life in humans. Based on these findings, AUVELITY may cause fetal harm when administered to pregnant women (see Data).

The available clinical data on the use of AUVELITY during pregnancy is insufficient to evaluate for a drug-associated risk of major birth malformations, miscarriage, or other adverse maternal or fetal outcomes. However, there are available data on one of the individual components of AUVELITY, bupropion. Data from epidemiological studies of pregnant women exposed to bupropion in the first trimester have not identified an increased risk of congenital malformations overall (see Data). There are risks to the mother associated with untreated depression in pregnancy (see Clinical Considerations).

The estimated background risk of major birth defects and miscarriage for the indicated population is unknown. All pregnancies have a background risk of birth defect, loss, or other adverse outcomes. In the U.S. general population, the estimated background risk of major birth defects and miscarriage in clinically recognized pregnancies is 2% to 4% and 15% to 20%, respectively.

Clinical Considerations

Disease-Associated Maternal and/or Embryo/Fetal Risk

A prospective, longitudinal study followed 201 pregnant women with a history of major depressive disorder who were euthymic and taking antidepressants during pregnancy at the beginning of pregnancy. The women who discontinued antidepressants during pregnancy were more likely to experience a relapse of major depression than women who continued antidepressants. Consider the risks to the mother of untreated depression and potential effects on the fetus when discontinuing or changing treatment with antidepressant medications during pregnancy and postpartum.

Data

Human Data

Bupropion

Data from the international bupropion Pregnancy Registry (675 first trimester exposures) and a retrospective cohort study using the United Healthcare database (1,213 first trimester exposures) did not show an increased risk for malformations overall. The Registry was not designed or powered to evaluate specific defects but suggested a possible increase in cardiac malformations.

No increased risk for cardiovascular malformations overall has been observed after bupropion exposure during the first trimester. The prospectively observed rate of cardiovascular malformations in pregnancies with exposure to bupropion in the first trimester from the international bupropion Pregnancy Registry was 1.3% (9 cardiovascular malformations/675 first trimester maternal bupropion exposures), which is similar to the background rate of cardiovascular malformations (approximately 1%). Data from the United Healthcare database, which had a limited number of exposed cases with cardiovascular malformations, and a case-control study (11,700 infants with cardiovascular malformations and 20,093 infants with non-cardiovascular malformations) of self-reported antidepressant use, including bupropion (n=728), from the National Birth Defects Prevention Study (NBDPS) did not show an increased risk for cardiovascular malformations overall after bupropion exposure during the first trimester.

Study findings on bupropion exposure during the first trimester and risk for left ventricular outflow tract obstruction (LVOTO) or ventricular septal defect (VSD) are inconsistent and do not allow conclusions regarding a possible association. The United Healthcare database lacked sufficient power to evaluate the LVOTO association. NBDPS found slightly increased risk for LVOTO after partially accounting for underlying maternal conditions (n = 14; adjusted odds ratio [OR] = 1.18; 95% CI: 0.58, 2.43), and the Slone Epidemiology case control study did not find increased risk for LVOTO.

The Slone Epidemiology Study found an increased risk for VSD following first trimester maternal bupropion exposure (n = 17; adjusted OR = 2.5; 95% CI: 1.3, 5.0) but did not find increased risk for any other cardiovascular malformations studied (including LVOTO as above). The NBDPS and United Healthcare database study did not find an association between first trimester maternal bupropion exposure and VSD.

For the findings of LVOTO and VSD, the studies were limited by the small number of exposed cases, inconsistent findings among studies, and the potential for chance findings from multiple comparisons in case control studies.

Animal Data

In studies conducted in pregnant mice, dextromethorphan-bupropion was administered orally during the period of organogenesis at doses of 0-0, 26-57, 34-75, and 68-150 mg/kg/day, respectively. Administration of dextromethorphan-bupropion did not affect body weight, weight gain, food consumption, or pregnancy at any dose level and did not produce gross pathologic findings or placental or fetal findings at any dose level. The no-effect level for reproductive organ findings in mice was 68-150 mg/kg in both sexes, which is approximately 3.7/3.5 times the MRHD for AUVELITY on a mg/m^2 basis.

When dextromethorphan/quinidine was administered orally (0/0, 5/100, 15/100, and 50/100 mg/kg/day) to pregnant rats during the period of organogenesis, embryo-fetal deaths were observed at the highest dose tested and reduced skeletal ossification was observed at all doses. Oral administration to pregnant rabbits during organogenesis in two separate studies (0/0, 5/60, 15/60, and 30/60 mg/kg day; 0/0, 5/100, 15/100, and 50/100 mg/kg/day) resulted in an increased incidence of fetal malformations at all but the lowest dose tested.

When dextromethorphan/quinidine was orally administered to female rats during pregnancy and lactation in two separate studies (0/0, 5/100, 15/100, and 30/100 mg/kg/day; 0/0, 5/100, 15/100, and 50/100 mg/kg/day), pup survival and pup weight were decreased at all doses, and developmental delay was observed in offspring at the mid and high doses. A no-effect dose for adverse developmental effects was not identified.

When dextromethorphan/quinidine was orally administered (0/0, 5/50, 15/50, 25/50 mg/kg) to male and female rats on postnatal day (PND) 7, the highest dose resulted in neuronal death in brain (thalamus and medulla oblongata). PND 7 in rat corresponds to the third trimester of gestation through the first several months of life but may extend to approximately three years of age in humans.

In studies conducted in pregnant rats and rabbits, bupropion alone was administered orally during the period of organogenesis at doses of up to 450 and 150 mg/kg/day, respectively (approximately 21 and 14 times the MRHD, respectively, on a mg/m^2 basis). There was no evidence of fetal malformations in rats. When given to pregnant rabbits during organogenesis, non-dose–related increases in incidence of fetal malformations and skeletal variations were observed at the lowest dose tested (25 mg/kg/day, approximately 2 times the MRHD on a mg/m^2 basis) and greater. Decreased fetal weights were observed at doses of 50 mg/kg/day (approximately 5 times the MRHD on a mg/m^2 basis) and greater. No maternal toxicity was evident at doses of 50 mg/kg/day or less. In a pre- and postnatal development study, bupropion administered orally to pregnant rats at doses of up to 150 mg/kg/day (approximately 7 times the MRHD on a mg/m^2 basis) from embryonic implantation through lactation had no effect on pup growth or development.

8.2 Lactation

Risk Summary

Data from published literature report the presence of bupropion and its metabolites in human milk (see Data). There are no data on the effects of bupropion or its metabolites on milk production. Limited data from postmarketing reports of bupropion use in lactating patients have not identified a clear association of adverse reactions in the breastfed infant.

Neurotoxicity findings were observed in juvenile rats treated with a combination of dextromethorphan/quinidine on postnatal day (PND) 7, which corresponds to the third trimester of gestation through the first few months of life and may extend through the first three years of life in humans [see Use in Specific Populations (8.1)]. It is not known whether dextromethorphan is present in human milk. There are no data on the effects of dextromethorphan on the breastfed infant or the effects on milk production. Because of the potential for neurotoxicity, advise patients that breastfeeding is not recommended during treatment with AUVELITY and for 5 days following final dose.

Data

In a lactation study of 10 women, levels of orally dosed bupropion and its active metabolites were measured in expressed milk. The average daily infant exposure (assuming 150 mL/kg daily consumption) to bupropion and its active metabolites was 2% of the maternal weight-adjusted dose. Postmarketing reports have described seizures in breastfed infants. The relationship of bupropion exposure and these seizures is unclear.

8.3 Females and Males of Reproductive Potential

Based on animal studies, AUVELITY may cause fetal harm when administered during pregnancy [see Warnings and Precautions (5.9), Use in Specific Populations (8.1)]. However, the separate effect of dextromethorphan on developmental toxicity at the recommended clinical dose is unclear. Use alternative treatment for females who are planning to become pregnant.

8.4 Pediatric Use

The safety and effectiveness of AUVELITY have not been established in pediatric patients.

AUVELITY contains bupropion. Antidepressants, including bupropion, increase the risk of suicidal thoughts and behaviors in pediatric patients [see Boxed Warning, Warning and Precautions (5.1)].

8.5 Geriatric Use

Clinical studies with AUVELITY did not include patients 65 years of age and older to determine whether they respond differently than younger adult patients.

8.6 Renal Impairment

Dosage adjustment of AUVELITY is recommended in patients with moderate renal impairment (eGFR 30 to 59 mL/minute/1.73 m^2) [see Dosage and Administration (2.3), Clinical Pharmacology (12.3)]. The pharmacokinetics of AUVELITY have not been evaluated in patients with severe renal impairment. AUVELITY is not recommended in patients with severe renal impairment (eGFR 15 to 29 mL/minute/1.73 m^2).

8.7 Hepatic Impairment

No dose adjustment of AUVELITY is recommended in patients with mild (Child-Pugh A) or moderate hepatic impairment (Child-Pugh B) [see Clinical Pharmacology (12.3)]. The pharmacokinetics of AUVELITY have not been evaluated in patients with severe hepatic impairment (Child-Pugh C). AUVELITY is not recommended in patients with severe hepatic impairment.

8.8 CYP2D6 Poor Metabolizers

Dosage adjustment is recommended in patients known to be poor CYP2D6 metabolizers because these patients have higher dextromethorphan concentrations than extensive/intermediate CYP2D6 metabolizers [see Dosage and Administration (2.5), Clinical Pharmacology (12.3)].

9 DRUG ABUSE AND DEPENDENCE

9.1 Controlled Substance

AUVELITY contains dextromethorphan and bupropion which are not controlled substances.

9.2 Abuse

Abuse is the intentional, non-therapeutic use of a drug, even once, for its desirable psychological or physiological effects.

AUVELITY has not been systematically studied in animals or humans for its potential for abuse, tolerance, or physical dependence. However, AUVELITY is a combination product containing dextromethorphan and bupropion, and cases of dextromethorphan abuse have been reported.

While clinical studies with AUVELITY did not reveal drug-seeking behavior, these observations were not systematic and it is not possible to predict on the basis of this experience the extent to which AUVELITY will be misused, diverted, and/or abused once marketed. Therefore, patients with a history of drug abuse should be observed closely for signs of AUVELITY misuse or abuse (e.g., development of tolerance, increases in dose, drug-seeking behavior).

AUVELITY is intended for oral use only. Seizures and/or cases of death have been reported when bupropion has been administered intranasally or by parenteral injection.

Dextromethorphan

Dextromethorphan has not been systematically studied in animals or humans for its potential for abuse, tolerance, or physical dependence. Cases of dextromethorphan abuse have been reported, predominantly in adolescents.

Bupropion

Controlled clinical trials conducted in normal volunteers, in subjects with a history of multiple drug abuse, and in depressed subjects showed some increase in motor activity and agitation/excitement, often typical of central stimulant activity.

In a population of individuals experienced with drugs of abuse, a single oral dose of 400 mg of bupropion (approximately 1.9 times the maximum recommended daily dosage of AUVELITY) produced mild amphetamine-like activity as compared with placebo on the Morphine-Benzedrine Subscale of the Addiction Research Center Inventories (ARCI) and a score intermediate between placebo and amphetamine on the Liking Scale of the ARCI. These scales measure general feelings of euphoria and drug liking which are often associated with abuse potential.

Findings in clinical trials, however, are not known to reliably predict the abuse potential of drugs. Nonetheless, evidence from single-dose studies does suggest that the recommended daily dosage of bupropion when administered in divided doses is not likely to be significantly reinforcing to people who abuse amphetamines or CNS stimulants. However, higher doses (which could not be tested because of the risk of seizure) might be modestly attractive to those who abuse CNS stimulant drugs.

10 OVERDOSAGE

Human Experience

There is limited clinical study experience regarding human overdosage with AUVELITY. Overdosage information is based on experience with the individual components, dextromethorphan and bupropion. Metabolism of the dextromethorphan component of AUVELITY is inhibited by the bupropion component, such that overdose due to AUVELITY might be more severe or more persistent compared to overdose of dextromethorphan alone.

Dextromethorphan

Symptoms of dextromethorphan overdose include nausea, vomiting, stupor, coma, respiratory depression, seizures, tachycardia, hyperexcitability, and toxic psychosis. Other adverse effects include ataxia, nystagmus, dystonia, blurred vision, and changes in muscle reflexes. Dextromethorphan may cause serotonin syndrome, and this risk is increased by overdose, particularly if taken with other serotonergic agents, SSRIs or tricyclic antidepressants.

Bupropion

Overdoses of up to 30 grams or more of bupropion (approximately 143 times the maximum recommended dose of AUVELITY) have been reported. Seizure was reported in approximately one-third of all cases. Other serious reactions reported with overdoses of bupropion alone included hallucinations, loss of consciousness, mental status changes, sinus tachycardia, ECG changes such as conduction disturbances (including QRS prolongation) or arrhythmias, clonus, myoclonus, and hyperreflexia. Fever, muscle rigidity, rhabdomyolysis, hypotension, stupor, coma, and respiratory failure have been reported mainly when bupropion was part of multiple drug overdoses.

Although most patients recovered without sequelae, deaths associated with overdoses of bupropion alone have been reported in patients ingesting large doses of the drug. Multiple uncontrolled seizures, bradycardia, cardiac failure, and cardiac arrest prior to death were reported in these patients.

Overdosage Management

Treatment of dextromethorphan overdosage should be directed at symptomatic and supportive measures.

There are no known antidotes for bupropion. In case of an overdose, provide supportive care, including close medical supervision and monitoring. Consider the possibility of multiple drug overdose. Ensure an adequate airway, oxygenation, and ventilation. Monitor cardiac rhythm and vital signs. Induction of emesis is not recommended.

Consider contacting a Poison Center (1-800-222-1222) or a medical toxicologist for overdosage management recommendations for AUVELITY.

11 DESCRIPTION

AUVELITY is a combination of dextromethorphan hydrobromide, an uncompetitive NMDA receptor antagonist and sigma-1 receptor agonist, and bupropion hydrochloride, an aminoketone and CYP450 2D6 inhibitor.

The chemical name of dextromethorphan hydrobromide is morphinan, 3- methoxy-17-methyl-, (9α, 13α, 14α), hydrobromide monohydrate. Dextromethorphan hydrobromide has the empirical formula C18H25NO•HBr•H2O and a molecular weight of 370.33 (271.4 dextromethorphan base). The structural formula is:

Dextromethorphan hydrobromide powder is white or almost white, crystalline, and sparingly soluble in water.

The chemical name of bupropion hydrochloride is:(±)-1-(3-chlorophenyl)-2-[(1,1-dimethylethyl)amino]-1propanone hydrochloride. Bupropion hydrochloride has the empirical formula C13H18ClNO•HCl and a molecular weight of 276.2 (239.74 bupropion base). The structural formula is:

Bupropion hydrochloride powder is white and highly soluble in water.

AUVELITY is for oral administration and is available as round bilayer tablets. Each tablet contains 45 mg dextromethorphan hydrobromide (equivalent to 32.98 mg dextromethorphan base) in an immediate-release formulation and 105 mg bupropion hydrochloride (equivalent to 91.14 mg bupropion base) in an extended-release formulation. Each tablet contains the following inactive ingredients: carbomer homopolymer, colloidal silicon dioxide, crospovidone, glyceryl monocaprylocaprate, l-cysteine hydrochloride monohydrate, magnesium stearate, microcrystalline cellulose, polyvinyl alcohol, red iron oxide, sodium lauryl sulfate, stearic acid, talc, titanium dioxide, and yellow iron oxide.

12 CLINICAL PHARMACOLOGY

12.1 Mechanism of Action

Dextromethorphan is an uncompetitive antagonist of the NMDA receptor (an ionotropic glutamate receptor) and a sigma-1 receptor agonist. The mechanism of dextromethorphan in the treatment of MDD is unclear.

The mechanism of action of bupropion in the treatment of MDD is unclear; however, it may be related to noradrenergic and/or dopaminergic mechanisms. Bupropion increases plasma levels of dextromethorphan by competitively inhibiting cytochrome P450 2D6, which catalyzes a major biotransformation pathway for dextromethorphan. Bupropion is a relatively weak inhibitor of the neuronal reuptake of norepinephrine and dopamine and does not inhibit monoamine oxidase or the reuptake of serotonin.

12.2 Pharmacodynamics

Cardiac Electrophysiology

At the maximum recommended dose, AUVELITY does not prolong the QT interval to any clinically relevant extent.

12.3 Pharmacokinetics

AUVELITY is a combination of dextromethorphan and bupropion. Bupropion inhibits the metabolism of dextromethorphan via CYP2D6. Dextromethorphan when co-administered with bupropion displays nonlinear pharmacokinetics at steady state, with greater than dose-proportional changes in AUC and Cmax for varying doses of dextromethorphan [60 to 120 mg (0.67-1.33 times the maximum recommended dose of AUVELITY)] and less than dose-proportional changes for varying doses of bupropion [150 to 300 mg (0.71-1.43 times the maximum recommended dose of AUVELITY)].

Steady state plasma concentrations of dextromethorphan and bupropion when given as AUVELITY are achieved within 8 days. The accumulation ratios for dextromethorphan at steady state when given as AUVELITY are 20 and 32, respectively based on Cmax and AUC0- 12, compared to 1.3 and 1.4, respectively, for dextromethorphan given without bupropion. The accumulation ratios for bupropion at steady state are 1.1 and 1.5, respectively based on Cmax and AUC0-12.

Absorption

The median Tmax of dextromethorphan and bupropion when given as AUVELITY was 3 hours and 2 hours, respectively.

The Cmax of the hydroxybupropion metabolite occurred approximately 3 hours post-dose and was approximately 14 times the peak level of bupropion and its AUC0-12 was about 19 times that of bupropion. The Cmax of the erythrohydroxybupropion and threohydroxybupropion metabolites occurred approximately 4 hours post-dose and were approximately equal to and 5 times that of bupropion, respectively. The AUC0-12 values were 1.2 and 7 times that of bupropion, respectively.

Effect of Food

AUVELITY can be taken with or without food. Dextromethorphan Cmax and AUC0-12 were unchanged and decreased by 14%, respectively, and bupropion Cmax and AUC0-12 were increased by 3% and 6%, respectively, when AUVELITY was administered with food.

Distribution

The plasma protein binding of dextromethorphan is approximately 60-70% and bupropion is 84%. The extent of protein binding of the hydroxybupropion metabolite is similar to that for bupropion; whereas, the extent of protein binding of the threohydroxybupropion metabolite is about half that seen with bupropion.

Elimination

Following 8 days of administration of AUVELITY in extensive metabolizers, the mean elimination half-life of dextromethorphan was increased approximately 3-fold to 22 hours, as compared to dextromethorphan given without bupropion.

The mean elimination half-life of dextromethorphan and bupropion was 22 hours and 15 hours, respectively. The apparent elimination half-life of hydroxybupropion, erythrohydroxybupropion and threohydroxybupropion metabolites were approximately 35, 44 and 33 hours, respectively.

Metabolism

Dextromethorphan is primarily metabolized by CYP2D6 to dextrorphan. Bupropion is extensively metabolized with three active metabolites: hydroxybupropion, which is formed via hydroxylation of the tert-butyl group of bupropion, and the amino-alcohol isomers, threohydroxybupropion and erythrohydroxybupropion, which are formed via reduction of the carbonyl group. In vitro findings suggest that CYP2B6 is the principal isoenzyme involved in the formation of hydroxybupropion, while cytochrome P450 enzymes are not involved in the formation of threohydroxybupropion. Oxidation of the bupropion side chain results in the formation of a glycine conjugate of meta-chlorobenzoic acid, which is then excreted as the major urinary metabolite. The potency and toxicity of the metabolites relative to bupropion have not been fully characterized. However, it has been demonstrated in an antidepressant screening test in mice that hydroxybupropion is one-half as potent as bupropion, while threohydroxybupropion and erythrohydroxybupropion are 5-fold less potent than bupropion.

Excretion

In CYP2D6 extensive metabolizers, approximately 37-52% of the orally administered dose of dextromethorphan is recovered in the urine. Less than 2% of the administered dose is excreted as unchanged parent drug in the urine. In CYP2D6 poor metabolizers, approximately 45-83% of the administered dose is recovered in the urine. Approximately 26% of the administered dose is excreted as unchanged parent drug in the urine.

Following oral administration of 200 mg of ^14C-bupropion in humans, 87% and 10% of the radioactive dose were recovered in the urine and feces, respectively. Only 0.5% of the oral dose was excreted as unchanged bupropion.

Specific Populations

Geriatric Patients

The pharmacokinetics of AUVELITY have not been studied in patients 65 years or older.

Pediatric Patients

The pharmacokinetics of AUVELITY in pediatric patients have not been studied.

Male and Female/ Racial or Ethnic Groups

No significant pharmacokinetic differences based on sex and race have been observed for AUVELITY.

Patients with Renal Impairment, Patients with Hepatic Impairment, and CYP2D6 Poor Metabolizers

The effects of renal impairment, hepatic impairment, and CYP2D6 poor metabolizer status on the exposure to AUVELITY are summarized in Figure 1 [see Dosage and Administration (2.3, 2.5)].

Figure 1 Effects of Renal Impairment, Hepatic Impairment, and CYP2D6 Poor Metabolizer Status on AUVELITY PK

Results are based on plasma concentrations of AUVELITY after 8 days of twice daily dosing. Data are GMRs and 90% CIs. Reference = matched healthy subjects for renal and hepatic impairment studies, and extensive or ultra-extensive CYP2D6 metabolizers. AUC = area under the plasma concentration-time curve from zero to 12 hours; BUP = bupropion; CI = confidence interval; Cmax = maximum plasma concentration; DM = dextromethorphan; GMRs = geometric mean ratios; PK = pharmacokinetics.

Drug Interaction Studies

In Vitro Assessment of Drug Interactions

The potential for dextromethorphan and bupropion to inhibit or induce cytochrome P450 in vitro were evaluated in human liver microsomes.

Bupropion and its metabolites (hydroxybupropion, erythrohydroxybupropion, threohydroxybupropion) are inhibitors of CYP2D6. At therapeutically relevant concentrations dextromethorphan does not inhibit CYP1A2, CYP2B6, CYP2C8, CYP2C9, CYP2C19, CYP2D6, or CYP3A4. Dextromethorphan does not cause induction of CYP1A2, CYP3A4, or CYP2B6.

Dextromethorphan is a substrate of the human P-gp transporter. Dextromethorphan does not inhibit transporters at therapeutically relevant concentrations.

In Vivo Assessment of Drug Interactions

The effects of other drugs on the exposure to AUVELITY are summarized in Figure 2 [see Dosage and Administration (2.4)].

Figure 2 Effects of Co-administered Compounds on AUVELITY PK

Results are based on steady state plasma concentrations of twice daily dosing of AUVELITY. Data are GMRs and 90% CIs. AUC = area under the plasma concentration-time curve from zero to 12 hours; BUP = bupropion; CI = confidence interval; Cmax = maximum plasma concentration; DM = dextromethorphan; GMRs = geometric mean ratios; PK = pharmacokinetics.

Digoxin

Literature data showed that digoxin exposure was decreased when a single oral dose of 0.5-mg digoxin was administered 24 hours after a single oral dose of extended-release 150 mg bupropion in healthy volunteers.

13 NONCLINICAL TOXICOLOGY

13.1 Carcinogenesis, Mutagenesis, Impairment of Fertility

Carcinogenesis

In a 26-week carcinogenicity study in the Tg.rasH2 transgenic mouse, dextromethorphan at oral doses up to 100 mg/kg/day did not show any evidence of carcinogenic potential.

In a two-year carcinogenicity study in rats, dextromethorphan was administered at an oral dose of 50 mg/kg/day. No biologically significant tumor findings were observed. This dose is approximately 5.4 times the maximum recommended human dose (MRHD) of 90 mg/day on a mg/m^2 basis.

Lifetime carcinogenicity studies were performed in rats and mice at bupropion doses up to 300 and 150 mg/kg/day, respectively. These doses are approximately 13.9 and 3.5 times the MRHD, respectively, on a mg/m^2 basis. In the rat study there was an increase in nodular proliferative lesions of the liver at doses of 100 to 300 mg/kg/day (approximately 4.6 to 13.9 times the MRHD on a mg/m^2 basis); lower doses were not tested. The question of whether or not such lesions may be precursors of neoplasms of the liver is currently unresolved. Similar liver lesions were not seen in the mouse study, and no increase in malignant tumors of the liver and other organs was seen in either study.

Mutagenesis

Dextromethorphan was negative in in vitro (bacterial reverse mutation, chromosomal aberration in human lymphocytes) and in vivo (mouse micronucleus) assays.

Bupropion produced a positive response (2 to 3 times control mutation rate) in 2 of 5 strains in the Ames bacterial mutagenicity assay. Bupropion produced an increase in chromosomal aberrations in 1 of 3 in vivo rat bone marrow cytogenetic studies.

Impairment of fertility

When dextromethorphan was co-administered with quinidine orally (0/0, 5/100, 15/100, and 50/100 mg/kg/day) to male and female rats prior to and during mating, and continuing to Day 7 of gestation in females, no effect on fertility was observed up to the highest dose tested.

There were no effects on male and female fertility when rats were administered oral doses of bupropion up to 300 mg/kg/day (approximately 14 times the MRHD on a mg/m^2 basis) in females prior to mating and either through Day 13 of gestation or through lactation, and in males for 60 days prior to and through mating. However, doses of 200 mg/kg/day (approximately 9 times the MRHD on a mg/m^2 basis) or greater, caused transient ataxia or behavioral changes in adult female rats. There were also no adverse effects on fertility, reproduction, or growth and development of male or female offspring.

The effects on fertility of administering dextromethorphan and bupropion in combination are not known at this time.

14 CLINICAL STUDIES

The efficacy of AUVELITY for the treatment of MDD in adults was demonstrated in a placebo-controlled clinical study (Study 1, NCT04019704) and confirmatory evidence which included a second study comparing AUVELITY to bupropion hydrochloride sustained-release tablets (Study 2, NCT03595579).)

In Study 1, adult patients (18 to 65 years of age) who met the Diagnostic and Statistical Manual of Mental Disorders (DSM-5) criteria for MDD were randomized to receive AUVELITY (45 mg of dextromethorphan hydrobromide and 105 mg of bupropion hydrochloride) twice daily (N=156) or placebo twice daily (N=162) for 6 weeks. Patients in Study 1 had a median age of 41 years and were 67% female, 55% Caucasian, 35% Black, and 5% Asian.

The primary outcome measure was the change from baseline to Week 6 in the total score of the Montgomery-Asberg Depression Rating Scale (MADRS). The MADRS is a clinician-rated scale used to assess the severity of depressive symptoms. Patients are rated on 10 items to assess feelings of sadness, inner tension, reduced sleep or appetite, difficulty concentrating, lassitude, lack of interest, pessimism, and suicidality. Scores on the MADRS range from 0 to 60, with higher scores indicating more severe depression. AUVELITY was statistically significantly superior to placebo in improvement of depressive symptoms as measured by decrease in MADRS total score at Week 6 (see Table 4).

Table 4: Primary Efficacy Results for Change from Baseline in MADRS Total Score at Week 6 in Adult Patients with MDD
Study | Treatment Group | Mean Baseline Score (SD) | LS Mean Change from Baseline (SE) | LS Mean Differencea (95% CI)
Study 1 | AUVELITY (N=156) | 33.6 (4.4) | -15.9 (0.9) | -3.9 (-6.4, -1.4)
Study 1 | Placebo (N=162) | 33.2 (4.4) | -12.1 (0.9) | ---
SD=standard deviation; SE=standard error; LS Mean=least-squares mean; CI=confidence interval.
adrug – placebo

The change from baseline in MADRS total score by week in Study 1 is displayed in Figure 3. The change in MADRS total score from baseline to Week 1 and from baseline to Week 2 were pre-specified secondary efficacy endpoints. The difference between AUVELITY and placebo in change from baseline in MADRS total score was statistically significant at Week 1 and at Week 2.

Figure 3: Change from Baseline in MADRS Total Score by Week (Study 1)

SE = Standard Error

Examination of demographic subgroups by age, sex, and race did not suggest differences in response.

In Study 2, patients with MDD were randomized to receive AUVELITY or bupropion hydrochloride sustained-release tablets 105 mg twice daily for 6 weeks. The primary outcome measure was calculated by assessing the change from baseline in total MADRS score at each on-site visit from Week 1 to Week 6 and then taking the average of those scores. The results of the study demonstrated that dextromethorphan contributes to the antidepressant properties of AUVELITY.

16 HOW SUPPLIED/STORAGE AND HANDLING

AUVELITY (dextromethorphan hydrobromide and bupropion hydrochloride) extended-release tablets are beige, film-coated, round, bilayer tablets with “45/105” debossed on one side. AUVELITY is supplied in the following package configuration:

- Dextromethorphan hydrobromide 45mg/bupropion hydrochloride 105 mg:
  Bottles of 30 tablets, NDC 81968-045-30
- Dextromethorphan hydrobromide 45mg/bupropion hydrochloride 105 mg:
  Bottles of 60 tablets, NDC 81968-045-60

Store AUVELITY in original bottle at 20°C to 25°C (68°F to 77°F), excursions permitted to 15°C to 30°C (59°F to 86°F) [see USP Controlled Room Temperature].

17 PATIENT COUNSELING INFORMATION

Advise the patient to read the FDA-approved patient labeling (Medication Guide).

Suicidal Thoughts and Behaviors

Advise patients and caregivers to look for the emergence of suicidal ideation and behavior, especially early during treatment and when the dose is adjusted up or down, and instruct them to report such symptoms to the healthcare provider [see Boxed Warning, and Warnings and Precautions (5.1)]

Hypersensitivity

Advise patients that both immediate and delayed hypersensitivity reactions to AUVELITY could occur. Instruct patients to seek medical attention immediately if they experience symptoms indicative of hypersensitivity, such as skin rash, pruritus, hives, chest pain, edema, shortness of breath, arthralgia, myalgia, or fever after taking AUVELITY [see Contraindications (4)].

Seizure

Advise patients that AUVELITY can cause seizure and that excessive use or abrupt discontinuation of alcohol, benzodiazepines, antiepileptic drugs, or sedatives/hypnotics can increase the risk. Advise patients to minimize or avoid use of alcohol. Instruct patients to use AUVELITY as directed and to discontinue, and not restart, AUVELITY if they experience a seizure while on treatment [see Contraindications (4), Warnings and Precautions (5.2), Drug Interactions (7.1)].

Increased Blood Pressure and Hypertension

Advise patients that AUVELITY can cause increased blood pressure and hypertension and that the risk is increased if used with some other medications such as MAOIs and drugs that increase dopaminergic or noradrenergic activity [see Warnings and Precautions (5.3), Drug Interactions (7.1)].

Activation of Mania or Hypomania

Advise patients to observe for signs of activation of mania/hypomania and instruct them to report such symptoms to the healthcare provider [see Warnings and Precautions (5.4)].

Psychosis and Other Neuropsychiatric Reactions

Inform patients that changes in mood including delusions, hallucinations, psychosis, concentration disturbances, paranoia, and confusion have occurred with use of bupropion, a component of AUVELITY. Instruct patients to notify a healthcare provider if they experience such symptoms [see Warnings and Precautions (5.5), Adverse Reactions (6.2)].

Angle-closure Glaucoma

Patients should be advised that taking AUVELITY can cause mild pupillary dilation, which in susceptible individuals, can lead to an episode of angle-closure glaucoma [see Warnings and Precautions (5.6)].

Dizziness

Advise patients that AUVELITY may cause dizziness. Inform patients to take precautions to reduce the risk of falls, particularly for patients with motor impairment affecting gait or a history of falls. Caution patients about operating hazardous machinery, including motor vehicles, until they know how they will be affected by AUVELITY [see Warnings and Precautions (5.7), Adverse Reactions (6.1)].

Serotonin Syndrome

Caution patients about the risk of serotonin syndrome, particularly with the concomitant use of AUVELITY with SSRIs or tricyclic antidepressants. Instruct patients to contact their health care provider or report to the emergency room if they experience signs or symptoms of serotonin syndrome [see Warnings and Precautions (5.8), Drug Interactions (7.1)].

Embryo-fetal Toxicity

Advise pregnant females and females of reproductive potential of the potential risk to a fetus [see Warning and Precautions (5.9)]. Advise patients to notify their healthcare provider if they become pregnant or intend to become pregnant during therapy with AUVELITY. Advise patients that there is a pregnancy exposure registry that monitors pregnancy outcomes in women exposed to AUVELITY during pregnancy [see Use in Specific Populations (8.1)].

Lactation

Advise patients not to breastfeed during treatment with AUVELITY and for 5 days after the final dose [see Use in Specific Populations (8.2)].

Administration Information

Advise patients not to take more than two tablets in the same day and to allow at least an 8-hour interval between doses [see Dosage and Administration (2.2)].

Drug Interactions

Inform patients that AUVELITY increases the risk of drug interactions. Instruct patients to inform their healthcare provider about all the medications that they are taking before taking AUVELITY. Before taking any new medications, patients should tell their healthcare provider that they are taking AUVELITY.

Advise patients that AUVELITY can increase adverse neuropsychiatric reactions or reduce alcohol tolerance and to avoid or limit use of alcohol during treatment with AUVELITY [see Drug Interactions (7.1)].

Bupropion-Containing Products

Inform patients that AUVELITY contains bupropion which is an active ingredient in medications for other uses. Advise patients to inform their healthcare provider of all the medications that they are taking, including other bupropion-containing products [see Dosage and Administration (2.1), Warnings and Precautions (5.2, 5.3, 5.5), Drug Interactions (7.1)].

Dextromethorphan-Containing Products

Inform patients that AUVELITY contains dextromethorphan which is an active ingredient in medications for other uses. Advise patients to inform their healthcare provider of all the medications that they are taking, including other dextromethorphan-containing products [see Dosage and Administration (2.1), Warnings and Precautions (5.5, 5.8), Drug Interactions (7.1)].

Distributed by:

Axsome Therapeutics, Inc.
New York, NY 10007

AXSOME THERAPEUTICS and AUVELITY are trademarks or registered trademarks of Axsome Therapeutics, Inc. in the United States and other countries.

For patent information: www.axsome.com/IP

©2025 Axsome Therapeutics, Inc. All rights reserved.

AUV-USPI-003.000-20251119

MEDICATION GUIDE

AUVELITY® (aw - VEHL - ah- tee)
(dextromethorphan hydrobromide and bupropion hydrochloride)
extended-release tablets, for oral use

What is the most important information I should know about AUVELITY?

AUVELITY may cause serious side effects, including:

- Increased risk of suicidal thoughts and actions. AUVELITY and other antidepressant medicines may increase suicidal thoughts and actions in some children, adolescents, and young adults, especially within the first few months of treatment or when the dose is changed. AUVELITY is not for use in children.
  - Depression or other mental illnesses are the most important causes of suicidal thoughts or actions.
  How can I watch for and try to prevent suicidal thoughts and actions in myself or a family member?
  - Pay close attention to any changes, especially sudden changes in mood, behavior, thoughts, or feelings or if you develop suicidal thoughts or actions. This is very important when an antidepressant medicine is started or when the dose is changed.
  - Call your healthcare provider right away to report new or sudden changes in mood, behavior, thoughts, or feelings or if you develop suicidal thoughts or actions.
  - Keep all follow-up visits with your healthcare provider as scheduled. Call your healthcare provider between visits as needed, especially if you have concerns about symptoms.
  Call your healthcare provider or get emergency help right away if you have any of the following symptoms, especially if they are new, worse, or worry you:
  - thoughts about suicide or dying
  - new or worse depression
  - feeling very agitated or restless
  - trouble sleeping (insomnia)
  - attempts to commit suicide
  - new or worse anxiety
  - panic attacks
  - new or worse irritability
  - acting aggressive, being angry, or violent
  - an extreme increase in activity and talking (mania)
  - acting on dangerous impulses
  - other unusual changes in behavior or mood

What is AUVELITY?

AUVELITY is a prescription medicine used to treat a certain type of depression called Major Depressive Disorder (MDD) in adults.

It is not known if AUVELITY is safe and effective for use in children.

Auvelity is not approved for uses other than the treatment of MDD. The ingredients in Auvelity, bupropion and dextromethorphan, are the same ingredients found in some other medicines approved for other uses.

Do not take AUVELITY if you:

- have or had a seizure disorder
- have or had an eating disorder such as anorexia nervosa or bulimia
- have recently suddenly stopped drinking alcohol or use medicines called benzodiazepines, barbiturates, or anti-seizure medicines, and you have recently suddenly stopped taking them.
- take a monoamine oxidase inhibitor (MAOI)
- have stopped taking an MAOI in the last 14 days
- are being treated with the antibiotic linezolid or intravenous methylene blue
- are allergic to dextromethorphan, bupropion, or any of the ingredients in AUVELITY. See the end of this Medication Guide for a complete list of ingredients in AUVELITY.

Ask your healthcare provider or pharmacist if you are not sure if you take an MAOI or one of these medicines, including the antibiotic linezolid or intravenous methylene blue.

Do not start AUVELITY if you stopped taking an MAOI in the last 14 days.

Do not start taking an MAOI for at least 14 days after you stop treatment with AUVELITY.

Before taking AUVELITY, tell your healthcare provider about all your medical conditions, including if you:

- have or had seizures or convulsions
- have had a head injury
- have had a heart attack or have heart problems
- have a tumor in your nervous system (brain or spine)
- have had a stroke
- have low blood sugar
- have low sodium levels in your blood
- have liver problems
- have kidney problems
- drink a lot of alcohol
- abuse prescription medicines or street drugs
- have diabetes and take oral diabetes medicines or use insulin to control your blood sugar
- have high blood pressure
- have history of falls
- have or had bipolar disorder, or have a family history of bipolar disorder, suicide, or depression
- have high pressure in the eye (glaucoma)
- are pregnant or plan to become pregnant. AUVELITY may harm your unborn baby if you take AUVELITY during pregnancy. AUVELITY is not recommended during pregnancy.
  - Tell your healthcare provider right away if you become pregnant or think you are pregnant during treatment with AUVELITY. Your healthcare provider will prescribe another treatment for females who plan to become pregnant.
  - There is a pregnancy registry for females who are exposed to AUVELITY during pregnancy. The purpose of the registry is to collect information about the health of females exposed to AUVELITY and their baby. If you become pregnant during treatment with AUVELITY, talk to your healthcare provider about registering with the National Pregnancy Registry for Antidepressants at 1-844-405-6185 or visit online at https://womensmentalhealth.org/clinical-and-research-programs/pregnancyregistry/antidepressants/.
- are breastfeeding or plan to breastfeed. One of the ingredients in AUVELITY, bupropion, passes into your breast milk. Do not breastfeed during treatment with AUVELITY and for 5 days after the final dose.

Tell your healthcare provider about all the medicines you take, including prescription and over-the-counter medicines, vitamins, and herbal supplements.

AUVELITY and some other medicines may affect each other causing possible serious side effects. AUVELITY may affect the way other medicines work and other medicines may affect the way AUVELITY works.

Especially tell your healthcare provider if you take:

- other medicines containing bupropion or dextromethorphan
- medicines used to treat mood, anxiety, psychotic or thought disorders, including selective serotonin reuptake inhibitors (SSRIs)
- tricyclic antidepressants
- theophylline
- corticosteroids
- oral diabetes medicines or use insulin to control your blood sugar
- medicines to control appetite (anorectic)
- nicotine medicines to help you stop smoking
- street (illicit) drugs
- benzodiazepines, sedatives-hypnotics (sleep medicines), or opiates
- CNS stimulants

Ask your healthcare provider if you are not sure if you are taking any of these medicines. Your healthcare provider can tell you if it is safe to take AUVELITY with your other medicines.

Do not start or stop any other medicines during treatment with AUVELITY without talking to your healthcare provider first. Stopping AUVELITY suddenly may cause you to have serious side effects. See, “What are the possible side effects of AUVELITY?”

Know the medicines you take. Keep a list of them to show to your healthcare provider and pharmacist when you get a new medicine.

How should I take AUVELITY?

- Take AUVELITY exactly as your healthcare provider tells you to take it.
- Swallow AUVELITY tablets whole. Do not crush, chew, or divide AUVELITY tablets.
- AUVELITY may be taken with or without food.
- Take AUVELITY 1 time a day for 3 days, then increase your dose to 2 times a day (taken at least 8 hours apart).
- Do not take more than 2 AUVELITY tablets in 24 hours.
- If you miss a dose, do not take an extra dose to make up for the dose you missed. Wait and take your next dose at the regular time. Do not take more than 1 dose of AUVELITY at a time.
- If you take too much AUVELITY, call your poison control center at 1-800-222-1222 or go to the nearest hospital emergency room right away.

What should I avoid while taking AUVELITY?

- Limit or avoid using alcohol during treatment with AUVELITY. If you usually drink a lot of alcohol, talk with your healthcare provider before suddenly stopping. If you suddenly stop drinking alcohol, you may increase your chance of having seizures.
- Do not drive a car or use heavy machinery until you know how AUVELITY affects you. AUVELITY can affect your ability to do these things safely.

What are possible side effects of AUVELITY?

AUVELITY may cause serious side effects, including:

- See “What is the most important information I should know about AUVELITY”
- Seizures.There is a risk of seizures during treatment with AUVELITY. The risk is higher in people who:
  - take higher doses of AUVELITY
  - have certain medical problems
  - take AUVELITY with certain other medicines
  Do not take AUVELITY with other medicines unless your healthcare provider tells you to.
  If you have a seizure during treatment with AUVELITY, stop taking AUVELITY and call your healthcare provider right away. Do not take AUVELITY again if you have a seizure.
- Increases in blood pressure (hypertension). Some people may get high blood pressure during treatment with AUVELITY. Your healthcare provider should check your blood pressure before you start taking and during treatment with AUVELITY.
- Manic episodes. Manic episodes may happen in people with bipolar disorder who take AUVELITY. Symptoms may include:
  - greatly increased energy
  - severe trouble sleeping
  - racing thoughts
  - reckless behavior
  - unusually grand ideas
  - excessive happiness or irritability
  - talking more or faster than usual
- Unusual thoughts or behaviors. One of the ingredients in AUVELITY (bupropion), can cause unusual thoughts or behaviors, including delusions (believing you are someone else), hallucinations (seeing or hearing things that are not there), paranoia (feeling that people are against you), or feeling confused. If this happens to you, call your healthcare provider.
- Eye problems (angle-closure glaucoma). AUVELITY may cause a type of eye problem called angle-closure glaucoma in people with certain other eye conditions. You may want to undergo an eye examination to see if you are at risk and receive preventative treatment if you are. Call your healthcare provider if you have eye pain, changes in your vision, or swelling or redness in or around the eye.
- Dizziness. AUVELITY may cause dizziness which may increase your risk for falls.
- Serotonin syndrome. A potentially life-threatening problem called serotonin syndrome can happen when you take AUVELITY with certain other medicines. Call your healthcare provider or go to the nearest hospital emergency room right away if you have any of the following signs and symptoms of serotonin syndrome:
  - agitation
  - sweating
  - seeing or hearing things that are not there (hallucinations)
  - flushing
  - confusion
  - high body temperature (hyperthermia)
  - coma
  - shaking (tremors), stiff muscles, or muscle twitching
  - fast heartbeat
  - loss of coordination
  - changes in blood pressure
  - seizures
  - dizziness
  - nausea, vomiting, diarrhea

The most common side effects of AUVELITY include:

- dizziness
- headache
- diarrhea
- feeling sleepy
- dry mouth
- excessive sweating
- sexual function problems

These are not all the possible side effects of AUVELITY.

Call your doctor for medical advice about side effects. You may report side effects to FDA at 1-800-FDA-1088.

How should I store AUVELITY?

- Store AUVELITY at room temperature between 68°F to 77°F (20°C to 25°C).
- Keep AUVELITY and all medicines out of the reach of children.

General information about the safe and effective use of AUVELITY.

Medicines are sometimes prescribed for purposes other than those listed in a Medication Guide. Do not use AUVELITY for a condition for which it was not prescribed. Do not give AUVELITY to other people, even if they have the same symptoms you have. It may harm them. You can ask your pharmacist or healthcare provider for information about AUVELITY that is written for healthcare professionals.

If you take a urine drug screening test, AUVELITY may make the test result positive for amphetamines. If you tell the person giving you the drug screening test that you are taking AUVELITY, they can do a more specific drug screening test that should not have this problem.

What are the ingredients in AUVELITY?

Active ingredients: dextromethorphan hydrobromide, bupropion hydrochloride.

Inactive ingredients: l-cysteine hydrochloride monohydrate, carbomer homopolymer, microcrystalline cellulose, colloidal silicon dioxide, crospovidone, stearic acid, and magnesium stearate.

Distributed and Marketed by: Axsome Therapeutics, Inc. New York, NY 10007

AXSOME Therapeutics and AUVELITY are trademarks owned by Axsome Therapeutics, Inc. in the United States and other countries. The other brands listed are trademarks owned or licensed to their respective owners and are not owned by or licensed to AXSOME Therapeutics, Inc. The makers of these brands are not affiliated with and do not endorse AXSOME Therapeutics, Inc. or its products.

©2022 AXSOME Therapeutics, Inc.

For more information about AUVELITY, visit AUVELITY.com or call 1-866-496-AXSM (1-866-496-2976).

This Medication Guide has been approved by the U.S. Food and Drug Administration.

AUV-USMG-001.001-20221219

Issued: 12/2022

PRINCIPAL DISPLAY PANEL - NDC: 81968-045-30 - 30-count Bottle Label

Rx only

NDC 81968-045-30

Auvelity®

(dextromethorphan HBr and bupropion HCl)

extended-release tablets

45mg/105mg

Attention: Dispense with the accompanying Medication Guide.

30 Tablets

For oral use

PRINCIPAL DISPLAY PANEL - NDC: 81968-045-60 - 60-count Bottle Label

Rx only

NDC 81968-045-60

Auvelity®

(dextromethorphan HBr and bupropion HCl)

extended-release tablets

45mg/105mg

Attention: Dispense with the accompanying Medication Guide.

60 Tablets

For oral use

PRINCIPAL DISPLAY PANEL - NDC: 81968-045-31 - 30-count Physician Sample Bottle Label

Rx only

NDC 81968-045-31

Auvelity®

(dextromethorphan HBr and bupropion HCl)

extended-release tablets

45mg/105mg

Attention: Dispense with the accompanying Medication Guide.

Patient Sample

Not for Sale

30 Tablets

For oral use

PRINCIPAL DISPLAY PANEL - NDC: 81968-045-31 - 30-count Physician Sample Carton Label

Rx only

NDC 81968-045-31

Auvelity®

(dextromethorphan HBr and bupropion HCl)

extended-release tablets 45mg/105mg

Patient Sample

30 Tablets

For oral use

Dispense with Medication Guide

PRINCIPAL DISPLAY PANEL - NDC: 81968-045-14 - 14-count Physician Sample Bottle Label

Rx only

NDC 81968-045-14

Auvelity®

(dextromethorphan HBr and bupropion HCl)

extended-release tablets

45mg/105mg

Attention: Dispense with the accompanying Medication Guide.

Patient Sample

Not for Sale

14 Tablets

For oral use

PRINCIPAL DISPLAY PANEL - NDC: 81968-045-14 - 14-count Physician Sample Carton Label

Rx only

NDC 81968-045-31

Auvelity®

(dextromethorphan HBr and bupropion HCl)

extended-release tablets 45mg/105mg

Patient Sample

30 Tablets

For oral use

Dispense with Medication Guide